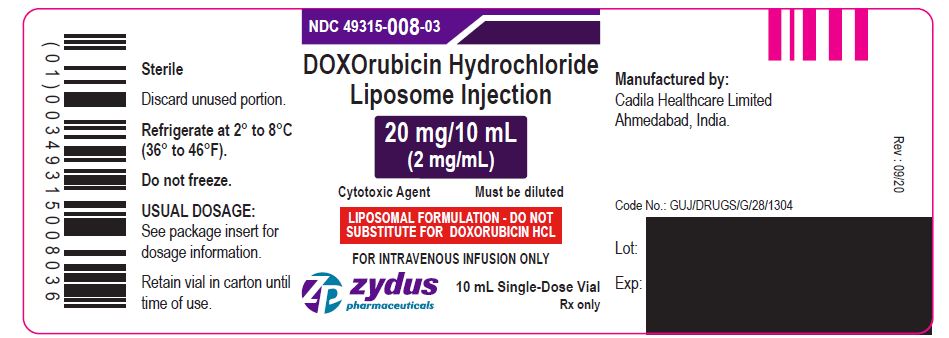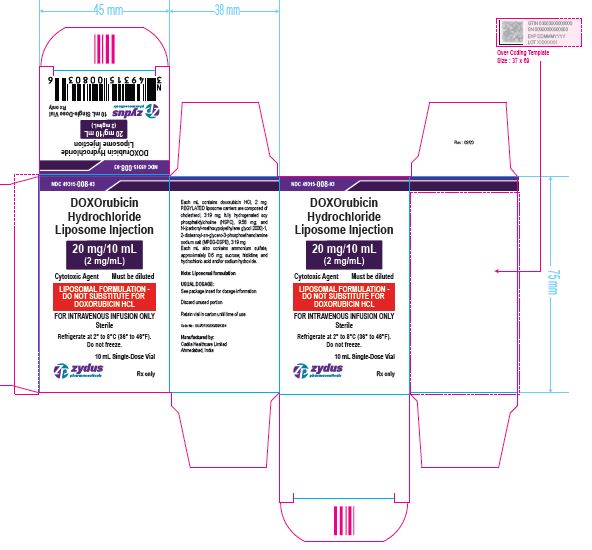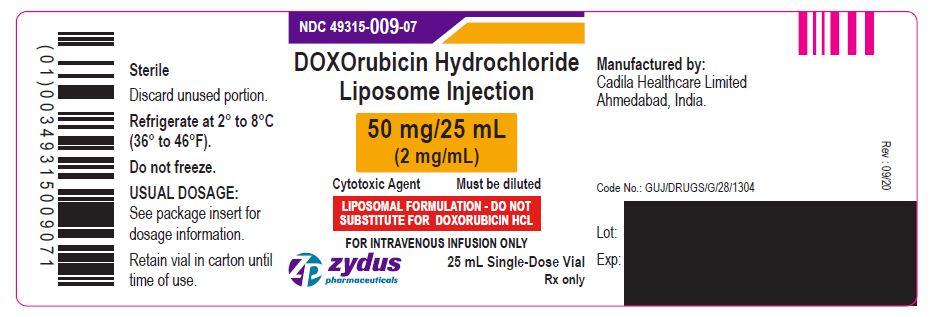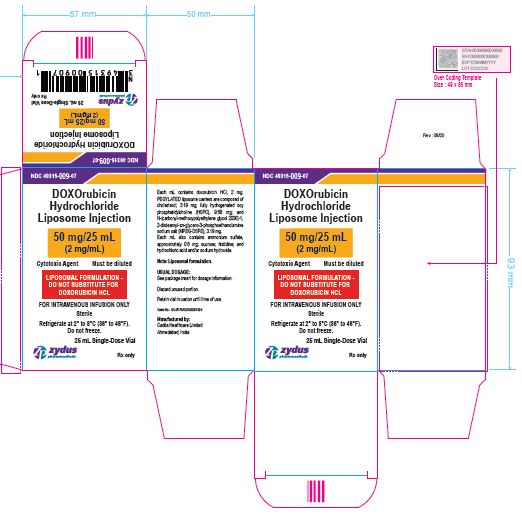 DRUG LABEL: DOXORUBICIN HYDROCHLORIDE
NDC: 49315-008 | Form: INJECTABLE, LIPOSOMAL
Manufacturer: Zydus Lifesciences Limited
Category: prescription | Type: HUMAN PRESCRIPTION DRUG LABEL
Date: 20221101

ACTIVE INGREDIENTS: DOXORUBICIN HYDROCHLORIDE 2 mg/1 mL
INACTIVE INGREDIENTS: N-(CARBONYL-METHOXYPOLYETHYLENE GLYCOL 2000)-1,2-DISTEAROYL-SN-GLYCERO-3-PHOSPHOETHANOLAMINE, SODIUM SALT 3.19 mg/1 mL; HYDROGENATED SOYBEAN LECITHIN 9.58 mg/1 mL; CHOLESTEROL 3.19 mg/1 mL; AMMONIUM SULFATE 0.6 mg/1 mL; SUCROSE; HISTIDINE; HYDROCHLORIC ACID; SODIUM HYDROXIDE

DOXOrubicin Hydrochloride Liposome Injection

PACKAGE LABEL.PRINCIPAL DISPLAY PANEL

20 mg/10 mL Container Label

NDC 49315-008-03

DOXOrubicin Hydrochloride Liposome Injection

20 mg/10 mL

(2 mg/mL)

Cytotoxic Agent Must be diluted

LIPOSOMAL FORMULATION – DO NOT SUBSTITUTE FOR DOXORUBICIN HCL

FOR INTRAVENOUS INFUSION ONLY

10 mL Single-Dose Vial

Rx only

20 mg/10 mL Carton Label

NDC 49315-008-03

DOXOrubicin Hydrochloride Liposome Injection

20 mg/10 mL

(2 mg/mL)

Cytotoxic Agent Must be diluted

LIPOSOMAL FORMULATION – DO NOT SUBSTITUTE FOR DOXORUBICIN HCL

FOR INTRAVENOUS INFUSION ONLY

Sterile

Refrigerate at 2⁰ to 8℃ (36⁰ to 46℉)

Do not freeze

10 mL Single-Dose Vial

Rx only

50 mg/25 mL Container Label

NDC 49315-009-07

DOXOrubicin Hydrochloride Liposome Injection

50 mg/25 mL

(2 mg/mL)

Cytotoxic Agent Must be diluted

LIPOSOMAL FORMULATION – DO NOT SUBSTITUTE FOR DOXORUBICIN HCL

FOR INTRAVENOUS INFUSION ONLY

25 mL Single-Dose Vial

Rx only

50 mg/25 mL Carton Label

NDC 49315-009-07

DOXOrubicin Hydrochloride Liposome Injection

50 mg/25 mL

(2 mg/mL)

Cytotoxic Agent Must be diluted

LIPOSOMAL FORMULATION – DO NOT SUBSTITUTE FOR DOXORUBICIN HCL

FOR INTRAVENOUS INFUSION ONLY

Sterile

Refrigerate at 2⁰ to 8℃ (36⁰ to 46℉)

Do not freeze

25 mL Single-Dose Vial

Rx only